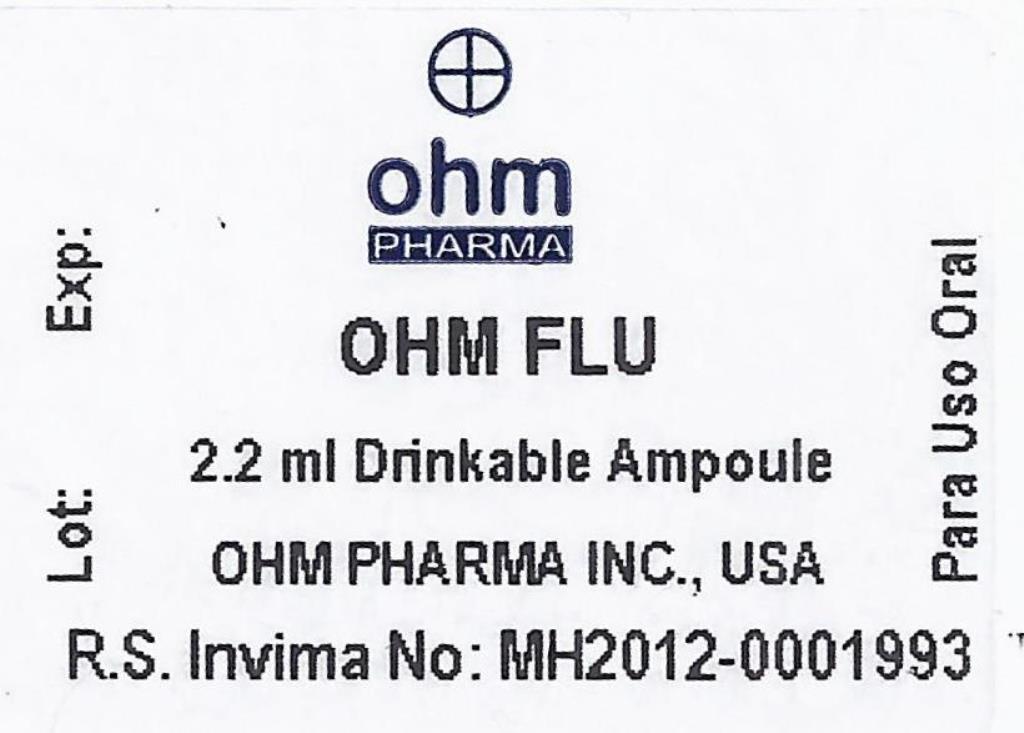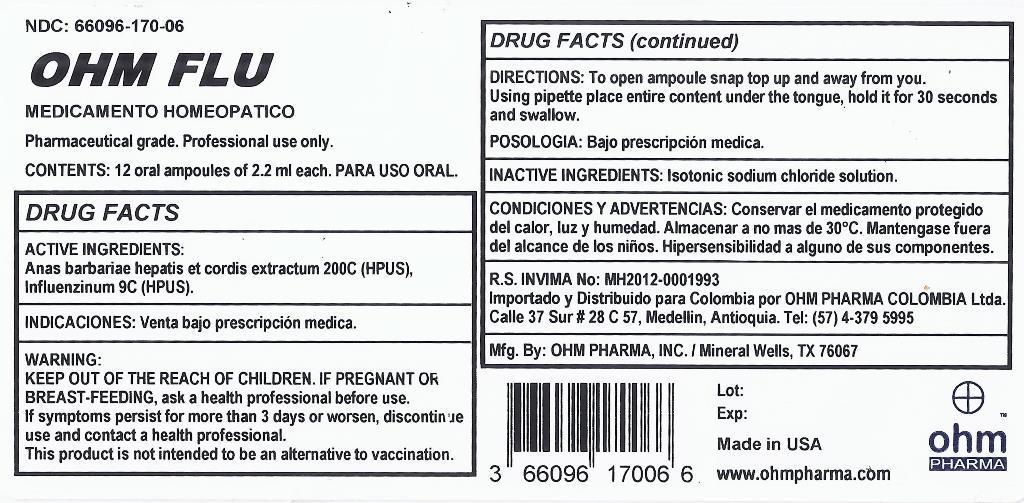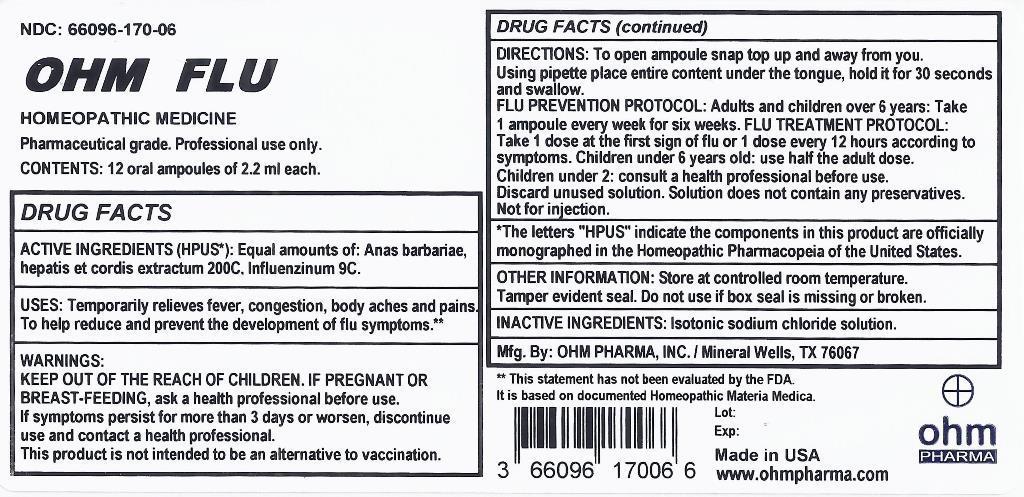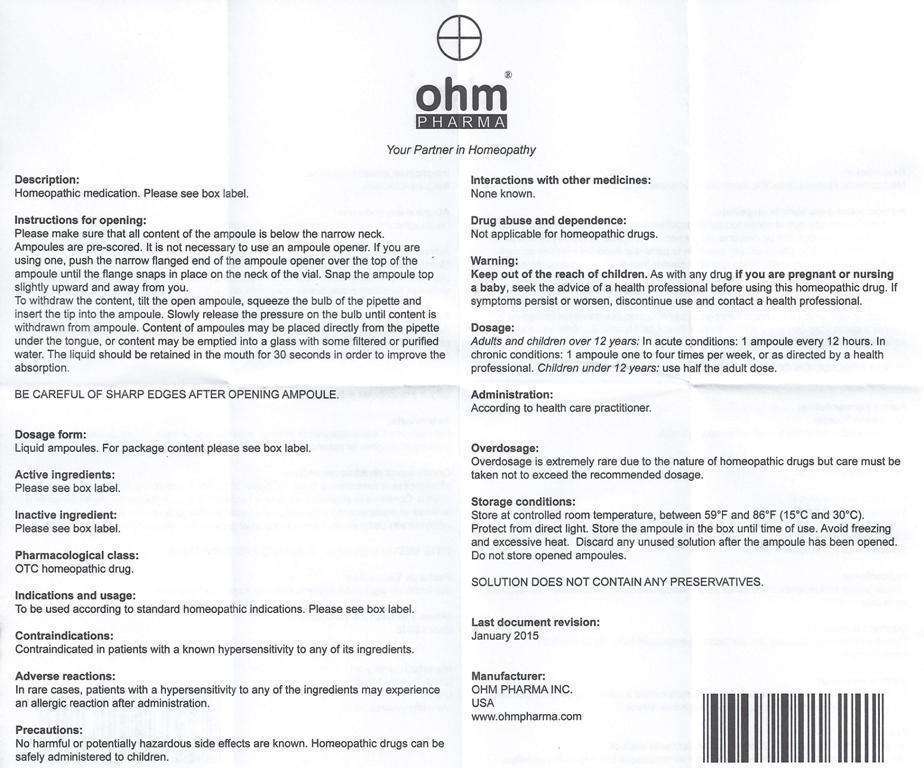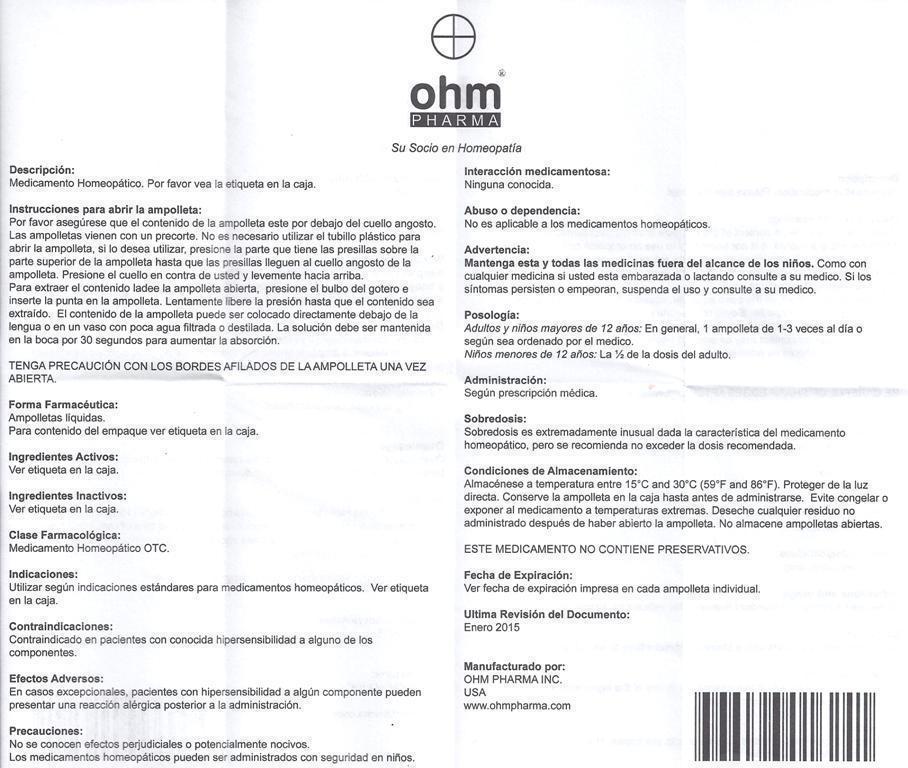 DRUG LABEL: OHM FLU
NDC: 66096-170 | Form: LIQUID
Manufacturer: OHM PHARMA INC.
Category: homeopathic | Type: HUMAN OTC DRUG LABEL
Date: 20211229

ACTIVE INGREDIENTS: CAIRINA MOSCHATA HEART/LIVER AUTOLYSATE 200 [hp_C]/1 mL; INFLUENZA A VIRUS 9 [hp_C]/1 mL; INFLUENZA B VIRUS 9 [hp_C]/1 mL
INACTIVE INGREDIENTS: SODIUM CHLORIDE

OHM FLU

ACTIVE INGREDIENT

ACTIVE INGREDIENTS (HPUS*): Equal amounts of: Anas barbariae, hepatis et cordis extractum 200C, Influenzinum 9C.

ACTIVE INGREDIENT

*The letters "HPUS" indicate the components in this product are officially monographed in the Homeopathic Pharmacopeia of the United States.

INDICATIONS AND USAGE

USES: Temporarily relieves relieves fever, congestion, body aches and pains. To help reduce and prevent the development of flu symptoms.**

**This statement has not been evaluated by the FDA.
It is based on documented Homeopathic Materia Medica.

WARNINGS:

IF PREGNANT OR BREAST-FEEDING, ask a health professional before use. If symptoms persist for more than 3 days, discontinue use and contact a health professional.

This product is not intended to be an alternative to vaccination.

KEEP OUT OF THE REACH OF CHILDREN.

DOSAGE AND ADMINISTRATION

DIRECTIONS: To open ampoule snap top up and away from you. Using pipette place entire content under the tongue, hold it for 30 seconds and swallow.

FLU PREVENTION PROTOCAL: Adults and children over 6 years: Take 1 ampoule every week for six weeks. FLU TREATMENT PROTOCOL: Take 1 dose at the first sign of flu or 1 dose every 12 hours according to symptoms. Children under 6 years old: use half the adult dose. Children under 2: consult a health professional before use.

Discard unused solution. Solution does not contain any preservatives.

Not for injection.

OTHER INFORMATION: Store at controlled room temperature. Tamper evident seal. Do not use if box seal is missing or broken.

INACTIVE INGREDIENTS: Isotonic sodium chloride solution.

QUESTIONS

Mfg. By: OHM PHARMA, INC. / Mineral Wells, TX 76067

Made in USA

www.ohmpharma.com

PURPOSE

Flu, fever, congestion, body aches and pains relief

PACKAGE LABEL

NDC: 66096-170-06

OHM FLU

HOMEOPATHIC MEDICINE

Pharmaceutical Grade. Professional use only.

CONTENTS: 12 oral ampoules of 2.2 ml each.